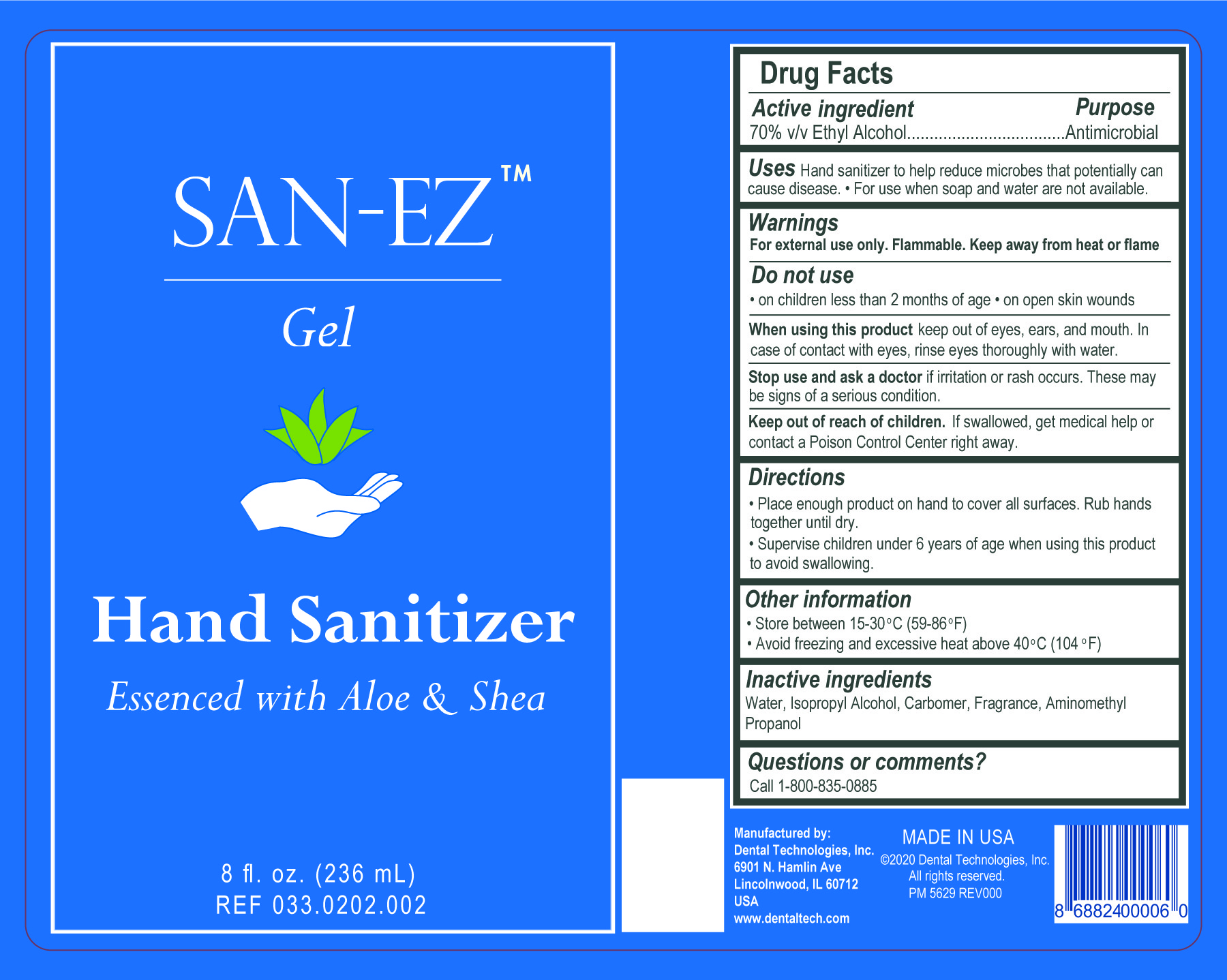 DRUG LABEL: San-EZ Hand Sanitizer
NDC: 55346-3302 | Form: GEL
Manufacturer: Dental Technologies, Inc.
Category: otc | Type: HUMAN OTC DRUG LABEL
Date: 20251104

ACTIVE INGREDIENTS: ALCOHOL 70 mL/100 mL
INACTIVE INGREDIENTS: TRICYCLODECENYL PROPIONATE; BENZYL ACETATE; ISOPROPYL ALCOHOL; LINALYL ACETATE; BENZYL SALICYLATE; 4-TERT-BUTYLCYCLOHEXYL ACETATE; BENZYL BENZOATE; LINALOOL, (+/-)-; .ALPHA.-HEXYLCINNAMALDEHYDE; DIMETHYL BENZYL CARBINOL; ACETYL CEDRENE; ACETYL HEXAMETHYL TETRALIN; CYCLAMEN ALDEHYDE; .BETA.-CITRONELLOL, (+/-)-; CITRAL; 2-METHYL-4-PHENYL-2-BUTANOL; CARBOMER 980; AMINOMETHYLPROPANOL; WATER

San-EZ Hand Sanitizer - Gel

Active ingredient

70% v/v Ethyl Alcohol

Purpose

Antimicrobial

Uses

Hand sanitizer to help reduce microbes that potentially can cause disease.

- For use when soap and water are not available.

Warnings

For external use only. Flammable. Keep away from heat or flame

Do not use

- on children less than 2 months of age
- on open skin wounds

When using this product

keep out of eyes, ears, and mouth. In case of contact with eyes, rinse eyes thoroughly with water.

Stop use and ask a doctor

if irritation or rash occures. These may be signs of a serious condition.

Keep out of reach of children.

If swallowed, get medical help or contact a Poison Control Center right away.

Directions

- Place enough product on hand to cover all surfaces. Rub hands together until dry.
- Supervise children under 6 years of age when using this product to avoid swallowing.

Other information

- Store between 15-30ºC (59-86ºF)
- Avoid freezing and excessive heat above 40ºC (104ºF)

Inactive ingredients

Water, Isopropyl Alcohol, Carbomer, Fragrance, Aminomethyl Propanol

Questions or comments?

Call 1-800-835-0885

Principal Display Panel

SAN-EZ™

Gel

Hand Sanitizer

Essened with Aloe & Shea

8 fl. oz. (236mL)

REF 033.0202.002